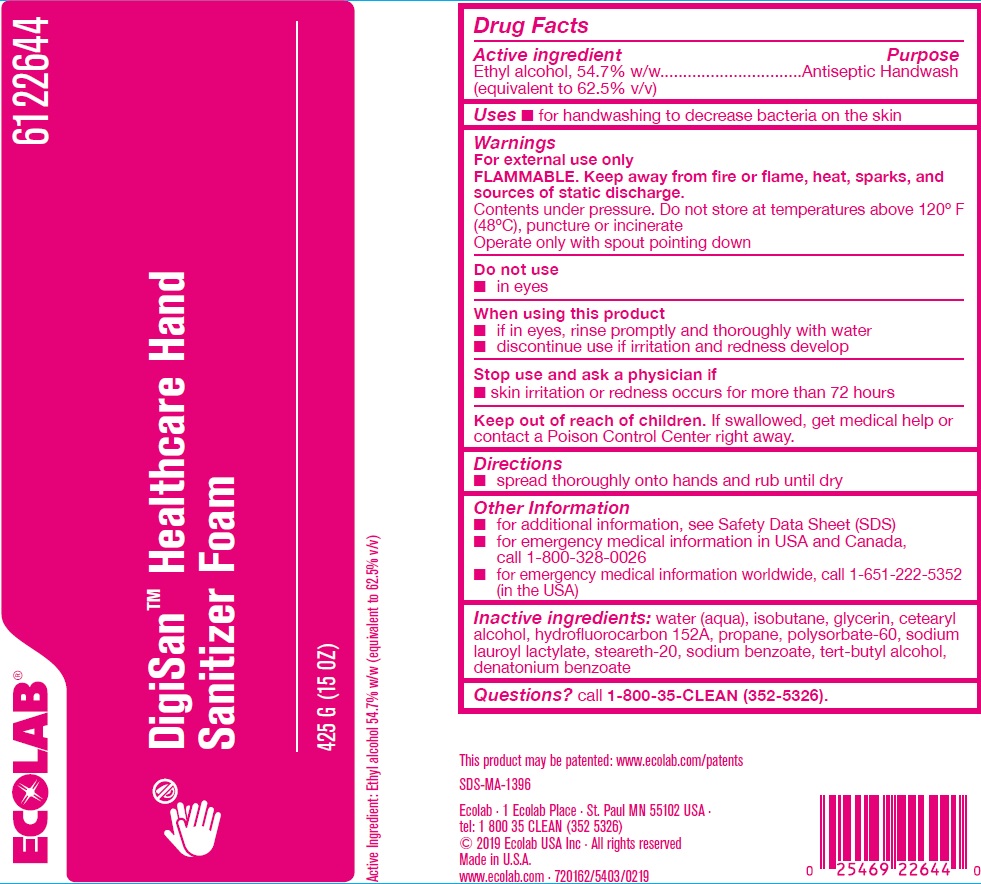 DRUG LABEL: DigiSan
NDC: 47593-618 | Form: AEROSOL, FOAM
Manufacturer: Ecolab Inc.
Category: otc | Type: HUMAN OTC DRUG LABEL
Date: 20251009

ACTIVE INGREDIENTS: ALCOHOL 0.547 mg/1 mg
INACTIVE INGREDIENTS: WATER; ISOBUTANE; GLYCERIN; CETOSTEARYL ALCOHOL; 1,1-DIFLUOROETHANE; PROPANE; POLYSORBATE 60; SODIUM LAUROYL LACTYLATE; STEARETH-20; SODIUM BENZOATE; TERT-BUTYL ALCOHOL; DENATONIUM BENZOATE

Drug Facts

Active ingredient

Active Ingredient: Ethyl alcohol 54.7% w/w (equivalent to 62.5% v/v)

Purpose

Antiseptic Handwash

Uses

- for handwashing to decrease bacteria on the skin

Warnings

For external use only
FLAMMABLE. Keep away from fire or flame, heat, sparks, and sources of static discharge
Contents under pressure. Do not store at temperatures above 120o F (48o C), puncture or incinerate
Operate only with spout pointing down

Do not use

- in eyes

When using this product

- if in eyes, rinse promptly and thoroughly with water
- discontinue use if irritation and redness develop

Stop use and ask a physician if

- skin irritation or redness occurs for more than 72 hours

KEEP OUT OF REACH OF CHILDREN

Keep out of reach children. If swallowed, get medical help or contact a Poison Control Center right away.

Directions

- spread thoroughly onto hands and rub until dry.

Other Information

- for additional information, see Safety Data Sheet (SDS)
- for emergency medical information in USA and Canada, call 1-800-328-0026
- for emergency medical information worldwide, call 1-651-222-5352 (in the USA)

INACTIVE INGREDIENT

Inactive ingredients: water (aqua), isobutane, glycerin, cetearyl alcohol, hydrofluorocarbon 152A, propane, polysorbate-60, sodium lauroyl lactylate, steareth-20, sodium benzoate, tert-butyl alcohol, denatonium benzoate.

Questions? call 1-800-35-CLEAN (352-5326).

Principal display panel and representative label

ECOLAB

6122644

DigiSan™ Healthcare Hand

Sanitizer Foam

425 G (15 OZ)

Active Ingredient: Ethyl alcohol 54.7% w/w (equivalent to 62.5% v/v)

This product may be patented: www.ecolab.com/patents

SDS-MA-1396

Ecolab - 1 Ecolab Place · St. Paul, MN 55102 USA ·

tel: 1 800 35 CLEAN (352 5326)

© 2019 Ecolab USA Inc · All Rights Reserved

Made in U.S.A.

www.ecolab.com · 720162/5403/0219